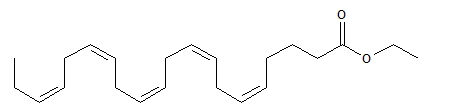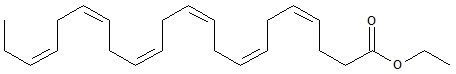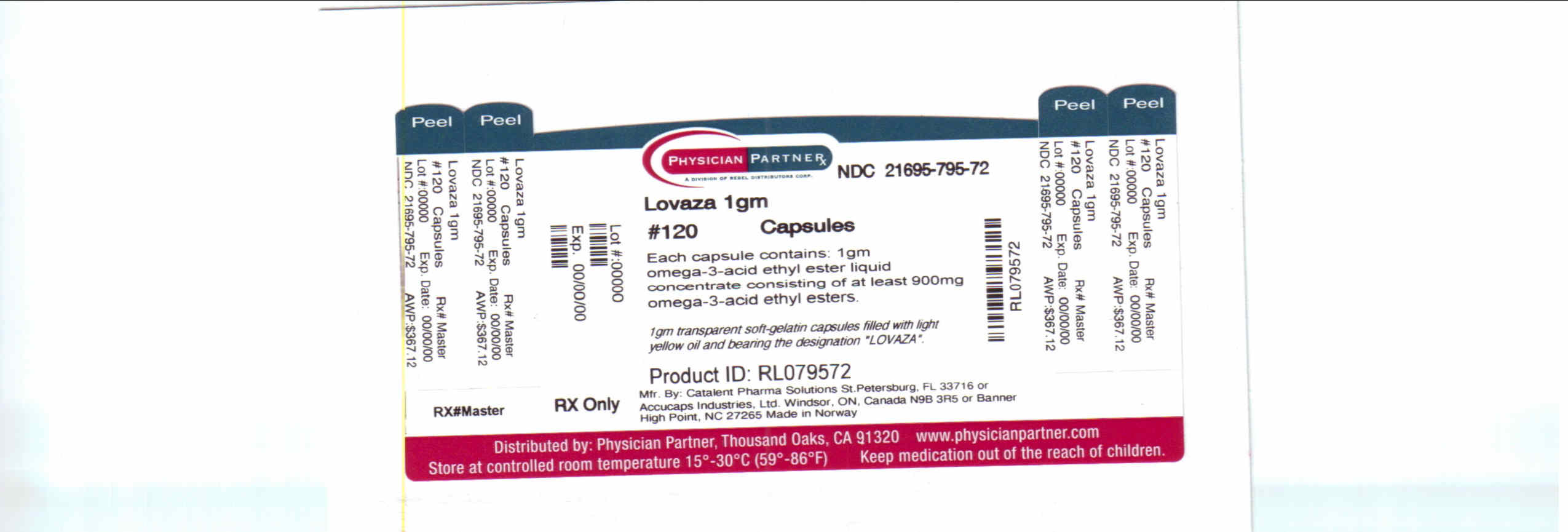 DRUG LABEL: LOVAZA
NDC: 21695-795 | Form: CAPSULE, LIQUID FILLED
Manufacturer: Rebel Distributors Corp
Category: prescription | Type: HUMAN PRESCRIPTION DRUG LABEL
Date: 20110104

ACTIVE INGREDIENTS: OMEGA-3-ACID ETHYL ESTERS 1 g/1 1
INACTIVE INGREDIENTS: ALPHA-TOCOPHEROL; GELATIN; GLYCERIN; WATER

HIGHLIGHTS OF PRESCRIBING INFORMATION

These highlights do not include all the information needed to use LOVAZA safely and effectively. See full prescribing information for LOVAZA.
LOVAZA® (omega-3-acid ethyl esters) Capsules
Initial U.S. Approval: 2004

1 INDICATIONS AND USAGE

LOVAZA is a combination of ethyl esters of omega 3 fatty acids, principally EPA and DHA, indicated as an adjunct to diet to reduce triglyceride (TG) levels in adult patients with severe (≥500 mg/dL) hypertriglyceridemia. (1)

Limitations of Use: The effect of LOVAZA on cardiovascular mortality and morbidity in patients with elevated triglycerides has not been determined. (1)

2 DOSAGE AND ADMINISTRATION

- The daily dose of LOVAZA is 4 grams per day taken as a single 4-gram dose (4 capsules) or as two 2-gram doses (2 capsules given twice daily). (2)
- Patients should be advised to swallow LOVAZA capsules whole. Do not break open, crush, dissolve or chew LOVAZA. (2)

3 DOSAGE FORMS AND STRENGTHS

1-gram transparent soft-gelatin capsules. (3)

4 CONTRAINDICATIONS

LOVAZA is contraindicated in patients with known hypersensitivity (e.g., anaphylactic reaction) to LOVAZA or any of its components. (4)

5 WARNINGS AND PRECAUTIONS

- In patients with hepatic impairment, monitor ALT and AST levels periodically during therapy. (5.1)
- LOVAZA may increase levels of LDL. Monitor LDL levels periodically during therapy. (5.1)
- Use with caution in patients with known hypersensitivity to fish and/or shellfish. (5.2)

6 ADVERSE REACTIONS

The most common adverse events (incidence >3% and greater than placebo) were eructation, infection, flu syndrome, and dyspepsia. (6)

To report SUSPECTED ADVERSE REACTIONS, contact GlaxoSmithKline at 1-888-825-5249 or FDA at 1-800-FDA-1088 or www.fda.gov/medwatch

7 DRUG INTERACTIONS

Omega-3-acids may prolong bleeding time. Patients taking LOVAZA and an anticoagulant or other drug affecting coagulation should be monitored periodically. (7.1)

8 USE IN SPECIFIC POPULATIONS

- Pregnancy: Use during pregnancy only if the potential benefit justifies the potential risk to the fetus. (8.1)
- Pediatric Use: The safety and effectiveness in pediatric patients have not been established. (8.4)

FULL PRESCRIBING INFORMATION

1 INDICATIONS AND USAGE

LOVAZA® (omega-3-acid ethyl esters) is indicated as an adjunct to diet to reduce triglyceride (TG) levels in adult patients with severe (≥500 mg/dL) hypertriglyceridemia.

Usage Considerations: Patients should be placed on an appropriate lipid-lowering diet before receiving LOVAZA and should continue this diet during treatment with LOVAZA.

Laboratory studies should be done to ascertain that the lipid levels are consistently abnormal before instituting LOVAZA therapy. Every attempt should be made to control serum lipids with appropriate diet, exercise, weight loss in obese patients, and control of any medical problems such as diabetes mellitus and hypothyroidism that are contributing to the lipid abnormalities. Medications known to exacerbate hypertriglyceridemia (such as beta blockers, thiazides, estrogens) should be discontinued or changed if possible prior to consideration of triglyceride-lowering drug therapy.

Limitations of Use: The effect of LOVAZA on cardiovascular mortality and morbidity in patients with elevated triglycerides has not been determined.

2 DOSAGE AND ADMINISTRATION

- Assess triglyceride levels carefully before initiating therapy. Identify other causes (e.g., diabetes mellitus, hypothyroidism, or medications) of high triglyceride levels and manage as appropriate. [see Indications and Usage (1)].
- Patients should be placed on an appropriate lipid-lowering diet before receiving LOVAZA, and should continue this diet during treatment with LOVAZA. In clinical studies, LOVAZA was administered with meals.

The daily dose of LOVAZA is 4 grams per day. The daily dose may be taken as a single 4-gram dose (4 capsules) or as two 2-gram doses (2 capsules given twice daily).

Patients should be advised to swallow LOVAZA capsules whole. Do not break open, crush, dissolve or chew LOVAZA.

3 DOSAGE FORMS AND STRENGTHS

LOVAZA (omega-3-acid ethyl esters) capsules are supplied as 1-gram transparent soft-gelatin capsules filled with light-yellow oil and bearing the designation LOVAZA.

4 CONTRAINDICATIONS

LOVAZA is contraindicated in patients with known hypersensitivity (e.g., anaphylactic reaction) to LOVAZA or any of its components.

5 WARNINGS AND PRECAUTIONS

5.1 Monitoring: Laboratory Tests

In patients with hepatic impairment, alanine aminotransferase (ALT) and aspartate aminotransferase (AST) levels should be monitored periodically during therapy with LOVAZA. In some patients, increases in ALT levels without a concurrent increase in AST levels were observed.

In some patients, LOVAZA increases LDL-C levels. LDL-C levels should be monitored periodically during therapy with LOVAZA.

Laboratory studies should be performed periodically to measure the patient’s TG levels during therapy with LOVAZA.

5.2 Fish Allergy

LOVAZA contains ethyl esters of omega-3 fatty acids (EPA and DHA) obtained from the oil of several fish sources. It is not known whether patients with allergies to fish and/or shellfish, are at increased risk of an allergic reaction to LOVAZA. LOVAZA should be used with caution in patients with known hypersensitivity to fish and/or shellfish.

6 ADVERSE REACTIONS

6.1 Clinical Trials Experience

Because clinical trials are conducted under widely varying conditions, adverse reaction rates observed in the clinical trials of a drug cannot be directly compared to rates in the clinical trials of another drug and may not reflect the rates observed in practice.

Adverse events reported in at least 1% of patients treated with LOVAZA 4 grams per day or placebo during 8 randomized, placebo-controlled, double-blind, parallel-group studies for HTG are listed in Table 1. Adverse events led to discontinuation of treatment in 3.5% of patients treated with LOVAZA and 2.6% of patients treated with placebo.

Table 1. Adverse Events in Randomized, Placebo-Controlled, Double-Blind, Parallel-Group Studies for Very High TG Levels (≥500 mg/dL) that used LOVAZA
BODY SYSTEM; Adverse Event* | LOVAZA; 4 grams/day; (N = 226) |  | Placebo; (N = 228)
BODY SYSTEM; Adverse Event* | n | % | n | %
Subjects with at least 1 adverse event | 80 | 35.4 | 63 | 27.6
Body as a whole
Infection | 10 | 4.4 | 5 | 2.2
Flu syndrome | 8 | 3.5 | 3 | 1.3
Back pain | 5 | 2.2 | 3 | 1.3
Pain | 4 | 1.8 | 3 | 1.3
Cardiovascular
Angina pectoris | 3 | 1.3 | 2 | 0.9
Digestive
Eructation | 11 | 4.9 | 5 | 2.2
Dyspepsia | 7 | 3.1 | 6 | 2.6
Skin
Rash | 4 | 1.8 | 1 | 0.4
Special senses
Taste perversion | 6 | 2.7 | 0 | 0.0

* Adverse events were coded using COSTART, version 5.0. Subjects were counted only once for each body system and for each preferred term.

Additional adverse events reported by 1 or more patients from clinical studies for HTG are listed below:

Body as a Whole: Enlarged abdomen, asthenia, body odor, chest pain, chills, suicide, fever, generalized edema, fungal infection, malaise, neck pain, neoplasm, rheumatoid arthritis, and sudden death.

Cardiovascular System: Arrhythmia, bypass surgery, cardiac arrest, hyperlipemia, hypertension, migraine, myocardial infarct, myocardial ischemia, occlusion, peripheral vascular disorder, syncope, and tachycardia.

Digestive System: Anorexia, constipation, dry mouth, dysphagia, colitis, fecal incontinence, gastritis, gastroenteritis, gastrointestinal disorder, increased appetite, intestinal obstruction, melena, pancreatitis, tenesmus, and vomiting.

Hematologic-Lymphatic System: Lymphadenopathy.

Infections and Infestations: Viral infection.

Metabolic and Nutritional Disorders: Edema, hyperglycemia, increased ALT, and increased AST.

Musculoskeletal System: Arthralgia, arthritis, myalgia, pathological fracture, and tendon disorder.

Nervous System: Central nervous system neoplasia, depression, dizziness, emotional lability, facial paralysis, insomnia, vasodilatation, and vertigo.

Respiratory System: Asthma, bronchitis, increased cough, dyspnea, epistaxis, laryngitis, pharyngitis, pneumonia, rhinitis, and sinusitis.

Skin: Alopecia, eczema, pruritus, and sweating.

Special Senses: Cataract.

Urogenital System: Cervix disorder, endometrial carcinoma, epididymitis, and impotence.

6.2 Postmarketing Experience

In addition to adverse reactions reported from clinical trials, the events described below have been identified during post-approval use of LOVAZA. Because these events are reported voluntarily from a population of unknown size, it is not possible to reliably estimate their frequency or to always establish a causal relationship to drug exposure.

The following events have been reported: anaphylactic reaction, hemorrhagic diathesis.

7 DRUG INTERACTIONS

7.1 Anticoagulants or Other Drugs Affecting Coagulation

Some studies with omega-3-acids demonstrated prolongation of bleeding time. The prolongation of bleeding time reported in these studies has not exceeded normal limits and did not produce clinically significant bleeding episodes. Clinical studies have not been done to thoroughly examine the effect of LOVAZA and concomitant anticoagulants. Patients receiving treatment with LOVAZA and an anticoagulant or other drug affecting coagulation should be monitored periodically (e.g., aspirin, NSAIDS, warfarin, coumarin).

8 USE IN SPECIFIC POPULATIONS

8.1 Pregnancy

Pregnancy Category C: There are no adequate and well-controlled studies in pregnant women. It is unknown whether LOVAZA can cause fetal harm when administered to a pregnant woman or can affect reproductive capacity. LOVAZA should be used during pregnancy only if the potential benefit to the patient justifies the potential risk to the fetus.

Animal Data

Omega-3-acid ethyl esters have been shown to have an embryocidal effect in pregnant rats when given in doses resulting in exposures 7 times the recommended human dose of 4 grams/day based on a body surface area comparison.

In female rats given oral gavage doses of 100, 600, and 2,000 mg/kg/day beginning 2 weeks prior to mating and continuing through gestation and lactation, no adverse effects were observed in the high dose group (5 times human systemic exposure following an oral dose of 4 grams/day based on body surface area comparison).

In pregnant rats given oral gavage doses of 1,000, 3,000, and 6,000 mg/kg/day from gestation day 6 through 15, no adverse effects were observed (14 times human systemic exposure following an oral dose of 4 grams/day based on a body surface area comparison).

In pregnant rats given oral gavage doses of 100, 600, and 2,000 mg/kg/day from gestation day 14 through lactation day 21, no adverse effects were seen at 2,000 mg/kg/day (5 times the human systemic exposure following an oral dose of 4 grams/day based on a body surface area comparison). However, decreased live births (20% reduction) and decreased survival to postnatal day 4 (40% reduction) were observed in a dose-ranging study using higher doses of 3,000 mg/kg/day (7 times the human systemic exposure following an oral dose of 4 grams/day based on a body surface area comparison).

In pregnant rabbits given oral gavage doses of 375, 750, and 1,500 mg/kg/day from gestation day 7 through 19, no findings were observed in the fetuses in groups given 375 mg/kg/day (2 times human systemic exposure following an oral dose of 4 grams/day based on a body surface area comparison). However, at higher doses, evidence of maternal toxicity was observed (4 times human systemic exposure following an oral dose of 4 grams/day based on a body surface area comparison).

8.3 Nursing Mothers

It is not known whether omega-3-acid ethyl esters are excreted in human milk. Because many drugs are excreted in human milk, caution should be exercised when LOVAZA is administered to a nursing woman.

8.4 Pediatric Use

Safety and effectiveness in pediatric patients have not been established.

8.5 Geriatric Use

A limited number of patients older than 65 years were enrolled in the clinical studies of LOVAZA. Safety and efficacy findings in subjects older than 60 years did not appear to differ from those of subjects younger than 60 years.

9 DRUG ABUSE AND DEPENDENCE

LOVAZA does not have any known drug abuse or withdrawal effects.

10 OVERDOSAGE

In the event of an overdose, the patient should be treated symptomatically, and general supportive care measures instituted, as required.

11 DESCRIPTION

LOVAZA, a lipid-regulating agent, is supplied as a liquid-filled gel capsule for oral administration. Each 1-gram capsule of LOVAZA contains at least 900 mg of the ethyl esters of omega-3 fatty acids sourced from fish oils. These are predominantly a combination of ethyl esters of eicosapentaenoic acid (EPA - approximately 465 mg) and docosahexaenoic acid (DHA - approximately 375 mg).

The empirical formula of EPA ethyl ester is C22H34O2, and the molecular weight of EPA ethyl ester is 330.51. The structural formula of EPA ethyl ester is:

The empirical formula of DHA ethyl ester is C24H36O2, and the molecular weight of DHA ethyl ester is 356.55. The structural formula of DHA ethyl ester is:

LOVAZA capsules also contain the following inactive ingredients: 4 mg α-tocopherol (in a carrier of soybean oil), and gelatin, glycerol, and purified water (components of the capsule shell).

12 CLINICAL PHARMACOLOGY

12.1 Mechanism of Action

The mechanism of action of LOVAZA is not completely understood. Potential mechanisms of action include inhibition of acyl-CoA:1,2-diacylglycerol acyltransferase, increased mitochondrial and peroxisomal β-oxidation in the liver, decreased lipogenesis in the liver, and increased plasma lipoprotein lipase activity. LOVAZA may reduce the synthesis of triglycerides in the liver because EPA and DHA are poor substrates for the enzymes responsible for TG synthesis, and EPA and DHA inhibit esterification of other fatty acids.

12.3 Pharmacokinetics

In healthy volunteers and in patients with hypertriglyceridemia, EPA and DHA were absorbed when administered as ethyl esters orally. Omega-3-acids administered as ethyl esters (LOVAZA) induced significant, dose-dependent increases in serum phospholipid EPA content, though increases in DHA content were less marked and not dose-dependent when administered as ethyl esters.

Specific Populations

Age

Uptake of EPA and DHA into serum phospholipids in subjects treated with LOVAZA was independent of age (<49 years versus ≥49 years).

Gender

Females tended to have more uptake of EPA into serum phospholipids than males. The clinical significance of this is unknown.

Pediatric

Pharmacokinetics of LOVAZA in pediatric patients have not been established [see Use in Specific Populations (8.4)].

Renal or Hepatic Impairment

LOVAZA has not been studied in patients with renal or hepatic impairment.

Drug-Drug Interactions

Simvastatin

In a 14-day study of 24 healthy adult subjects, daily co-administration of simvastatin 80 mg with LOVAZA 4 grams did not affect the extent (AUC) or rate (Cmax) of exposure to simvastatin or the major active metabolite, beta-hydroxy simvastatin at steady state.

Atorvastatin

In a 14-day study of 50 healthy adult subjects, daily co-administration of atorvastatin 80 mg with LOVAZA 4 grams did not affect AUC or Cmax of exposure to atorvastatin, 2-hydroxyatorvastatin, or 4-hydroxyatorvastatin at steady state.

Rosuvastatin

In a 14-day study of 48 healthy adult subjects, daily co-administration of rosuvastatin 40 mg with LOVAZA 4 grams did not affect AUC or Cmax of exposure to rosuvastatin at steady state.

In vitro studies using human liver microsomes indicated that clinically significant cytochrome P450 mediated inhibition by EPA/DHA combinations are not expected in humans.

13 NONCLINICAL TOXICOLOGY

13.1 Carcinogenesis, Mutagenesis, Impairment of Fertility

In a rat carcinogenicity study with oral gavage doses of 100, 600, and 2,000 mg/kg/day, males were treated with omega-3-acid ethyl esters for 101 weeks and females for 89 weeks without an increased incidence of tumors (up to 5 times human systemic exposures following an oral dose of 4 grams/day based on a body surface area comparison). Standard lifetime carcinogenicity bioassays were not conducted in mice.

Omega-3-acid ethyl esters were not mutagenic or clastogenic with or without metabolic activation in the bacterial mutagenesis (Ames) test with Salmonella typhimurium and Escherichia coli or in the chromosomal aberration assay in Chinese hamster V79 lung cells or human lymphocytes. Omega-3-acid ethyl esters were negative in the in vivo mouse micronucleus assay.

In a rat fertility study with oral gavage doses of 100, 600, and 2,000 mg/kg/day, males were treated for 10 weeks prior to mating and females were treated for 2 weeks prior to and throughout mating, gestation, and lactation. No adverse effect on fertility was observed at 2,000 mg/kg/day (5 times human systemic exposure following an oral dose of 4 grams/day based on a body surface area comparison).

14 CLINICAL STUDIES

14.1 Severe Hypertriglyceridemia

The effects of LOVAZA 4 grams per day were assessed in 2 randomized, placebo-controlled, double-blind, parallel-group studies of 84 adult patients (42 on LOVAZA, 42 on placebo) with very high triglyceride levels. Patients whose baseline triglyceride levels were between 500 and 2,000 mg/dL were enrolled in these 2 studies of 6 and 16 weeks duration. The median triglyceride and LDL-C levels in these patients were 792 mg/dL and 100 mg/dL, respectively. Median HDL-C level was 23.0 mg/dL.

The changes in the major lipoprotein lipid parameters for the groups receiving LOVAZA or placebo are shown in Table 2.

Table 2. Median Baseline and Percent Change From Baseline in Lipid Parameters in Patients with Very High TG Levels (≥500 mg/dL)
Parameter | LOVAZA; N = 42 |  | Placebo; N = 42 |  | Difference
Parameter | BL | % Change | BL | % Change | Difference
TG | 816 | -44.9 | 788 | +6.7 | -51.6
Non-HDL-C | 271 | -13.8 | 292 | -3.6 | -10.2
TC | 296 | -9.7 | 314 | -1.7 | -8.0
VLDL-C | 175 | -41.7 | 175 | -0.9 | -40.8
HDL-C | 22 | +9.1 | 24 | 0.0 | +9.1
LDL-C | 89 | +44.5 | 108 | -4.8 | +49.3

BL = Baseline (mg/dL); % Change = Median Percent Change from Baseline; Difference = LOVAZA Median % Change – Placebo Median % Change

LOVAZA 4 grams per day reduced median TG, VLDL-C, and non-HDL-C levels and increased median HDL-C from baseline relative to placebo. Treatment with LOVAZA to reduce very high TG levels may result in elevations in LDL-C and non-HDL-C in some individuals. Patients should be monitored to ensure that the LDL-C level does not increase excessively.

The effect of LOVAZA on the risk of pancreatitis in patients with very high TG levels has not been evaluated.

The effect of LOVAZA on cardiovascular mortality and morbidity in patients with elevated TG levels has not been determined.

14.2 Other Clinical Experience

The effects of LOVAZA 4 grams per day as add-on therapy to treatment with simvastatin were evaluated in a randomized, placebo-controlled, double-blind, parallel-group study of 254 adult patients (122 on LOVAZA and 132 on placebo) with persistent high triglycerides (200 to 499 mg/dL) despite simvastatin therapy. Patients were treated with open-label simvastatin 40 mg per day for 8 weeks prior to randomization to control their LDL-C to no greater than 10% above NCEP ATP III goal and remained on this dose throughout the study. Following 8 weeks of open-label treatment with simvastatin, patients were randomized to either LOVAZA 4 grams per day or placebo for an additional 8 weeks with simvastatin co-therapy. The median baseline triglyceride and LDL-C levels in these patients were 268 mg/dL and 89 mg/dL, respectively. Median baseline non-HDL-C and HDL-C levels were 138 mg/dL and 45 mg/dL, respectively.

The changes in the major lipoprotein lipid parameters for the groups receiving LOVAZA plus simvastatin or placebo plus simvastatin are shown in Table 3.

Table 3. Response to the Addition of LOVAZA 4 grams per day to Ongoing Simvastatin 40 mg per day Therapy in Patients with High Triglycerides (200 to 499 mg/dL)
Parameter | LOVAZA + Simvastatin; N = 122 |  |  | Placebo + Simvastatin; N = 132 |  |  | Difference | P-Value
Parameter | BL | EOT | Median % Change | BL | EOT | Median % Change | Difference | P-Value
Non-HDL-C | 137 | 123 | -9.0 | 141 | 134 | -2.2 | -6.8 | <0.0001
TG | 268 | 182 | -29.5 | 271 | 260 | -6.3 | -23.2 | <0.0001
TC | 184 | 172 | -4.8 | 184 | 178 | -1.7 | -3.1 | <0.05
VLDL-C | 52 | 37 | -27.5 | 52 | 49 | -7.2 | -20.3 | <0.05
Apo-B | 86 | 80 | -4.2 | 87 | 85 | -1.9 | -2.3 | <0.05
HDL-C | 46 | 48 | +3.4 | 43 | 44 | -1.2 | +4.6 | <0.05
LDL-C | 91 | 88 | +0.7 | 88 | 85 | -2.8 | +3.5 | =0.05

BL = Baseline (mg/dL); EOT = End of Treatment (mg/dL); Median % Change = Median Percent Change from Baseline; Difference = LOVAZA Median % Change – Placebo Median % Change

LOVAZA 4 grams per day significantly reduced non-HDL-C, TG, TC, VLDL-C, and Apo-B levels and increased HDL-C and LDL-C from baseline relative to placebo.

16 HOW SUPPLIED/STORAGE AND HANDLING

LOVAZA (omega-3-acid ethyl esters) capsules are supplied as 1-gram transparent soft-gelatin capsules filled with light-yellow oil and bearing the designation LOVAZA.

Bottles of 120: NDC 21695-795-72

Store at 25°C (77°F); excursions permitted to 15° to 30°C (59° to 86°F) [see USP Controlled Room Temperature]. Do not freeze. Keep out of reach of children.

17 PATIENT COUNSELING INFORMATION

See FDA-approved patient labeling

- LOVAZA should be used with caution in patients with known sensitivity or allergy to fish and/or shellfish [see Warnings and Precautions (5.3)].
- Patients should be advised that use of lipid-regulating agents does not reduce the importance of adhering to diet [see Dosage and Administration (2)].
- Patients should be advised not to alter LOVAZA capsules in any way and to ingest intact capsules only [see Dosage and Administration (2)].

Manufactured for GlaxoSmithKline by:

Catalent Pharma Solutions

2725 Scherer Drive

St. Petersburg, FL 33716-1016

Accucaps Industries Limited

2125 Ambassador Drive

Windsor, Ontario, Canada N9B 3R5

Banner Pharmaceuticals Inc.

4125 Premier Drive

High Point, NC 27265

Distributed by:

GlaxoSmithKline

Research Triangle Park, NC 27709

LOVAZA is a registered trademark of the GlaxoSmithKline group of companies.

©2009 GlaxoSmithKline. All rights reserved.

September 2009 LVZ:5PI

PHARMACIST-DETACH HERE AND GIVE INSTRUCTIONS TO PATIENT

_ _ _ _ _ _ _ _ _ _ _ _ _ _ _ _ _ _ _ _ _ _ _ _ _ _ _ _ _ _ _ _ _ _ _ _ _ _ _ _ _ _ __ _ _ _ _ _ _ _

PATIENT INFORMATION

LOVAZA® (lō-vā-ză)

(omega-3-acid ethyl esters) Capsules

Read the Patient Information that comes with LOVAZA before you start taking it, and each time you get a refill. There may be new information. This leaflet does not take the place of talking with your doctor about your condition or treatment.

What is LOVAZA?

LOVAZA is a prescription medicine, called a lipid-regulating medicine, for adults. LOVAZA is made of omega-3 fatty acids from oils of fish, such as salmon and mackeral. Omega-3 fatty acids are substances that your body needs but cannot produce itself.

LOVAZA is used along with a low-fat and low-cholesterol diet to lower very high triglycerides (fats) in your blood. Before taking LOVAZA, talk to your healthcare provider about how you can lower high blood fats by:

- losing weight, if you are overweight
- increasing physical exercise
- lowering alcohol use
- treating diseases such as diabetes and low thyroid (hypothyroidism)
- adjusting the dose or changing other medicines that raise triglyceride levels such as certain blood pressure medicines and estrogens

Treatment with LOVAZA has not been shown to prevent heart attacks or strokes.

LOVAZA has not been studied in children under the age of 18 years.

Who should not take LOVAZA?

Do not take LOVAZA if you:

- are allergic to LOVAZA or any of its ingredients. See the end of this leaflet for a complete list of ingredients in LOVAZA.

What should I tell my doctor before taking LOVAZA?

Tell your doctor about all of your medical conditions, including if you:

- drink more than 2 glasses of alcohol daily.
- have diabetes.
- have a thyroid problem called hypothyroidism.
- have a liver problem.
- have a pancreas problem.
- are allergic to fish and/or shellfish. LOVAZA may not be right for you.
- are pregnant, or planning to become pregnant. It is not known if LOVAZA can harm your unborn baby.
- are breastfeeding. It is not known if LOVAZA passes into your milk and if it can harm your baby.

Tell your doctor about all the medicines you take, including prescription and non-prescription medicine, vitamins, and herbal supplements. LOVAZA and certain other medicines can interact. Especially tell your doctor if you take medicines that affect clotting such as anticoagulants or blood thinners. Examples of these medicines include aspirin, nonsteroidal anti-inflammatory agents (NSAIDS), warfarin, coumarin, and clopidogrel (PLAVIX®).

Know all the medicines you take. Keep a list of them with you to show your doctor and pharmacist.

How should I take LOVAZA?

- Take LOVAZA exactly as prescribed. Do not change your dose or stop LOVAZA without talking to your doctor.
- The usual dose of LOVAZA is 4 capsules:
  - Take all 4 capsules at the same time, or
  - Take 2 capsules two times a day
- Take LOVAZA at the same time or times each day.
- Take LOVAZA with or without food. You may find it easier to take LOVAZA with food.
- Do not take more than 4 capsules a day. Taking more than 4 capsules per day may increase the chance of side effects.
- Take LOVAZA capsules whole. Do not break, crush, dissolve, or chew LOVAZA capsules before swallowing. If you cannot swallow LOVAZA capsules whole, tell your doctor. You may need a different medicine.
- Your doctor should start you on a low-fat and low-cholesterol diet before giving you LOVAZA. Stay on this low-fat and low-cholesterol diet while taking LOVAZA.
- Your doctor should do blood tests to check your triglyceride and cholesterol levels during treatment with LOVAZA.
- If you have liver disease, your doctor should do blood tests to check your liver function during treatment with LOVAZA.
- If you miss a dose of LOVAZA, take it as soon as you remember. However, if you miss one day of LOVAZA, do not double your dose when you next take it.
- If you take too much LOVAZA or overdose, call your doctor or Poison Control Center right away.

What are the possible side effects of LOVAZA?

The most common side effects with LOVAZA are burping, infection, flu symptoms, upset stomach, a change in your sense of taste, back pain, and skin rash.

LOVAZA may affect certain blood tests. It may change:

- one of the tests to check liver function (ALT)
- one of the tests to measure cholesterol levels (LDL-C)

Talk to your doctor if you have side effects that bother you or that will not go away. You may report side effects to FDA at 1-800-FDA-1088.

These are not all the side effects with LOVAZA. For more information, ask your doctor or pharmacist.

How should I store LOVAZA?

- Store LOVAZA at room temperature, 59° to 86° F (15° to 30° C). Do not freeze.
- Do not keep medicine that is out of date or that you no longer need.
- Keep LOVAZA out of the reach of children. Be sure that if you throw medicines away, it is out of the reach of children.

General information about LOVAZA

Medicines are sometimes prescribed for conditions that are not mentioned in patient information leaflets. Do not use LOVAZA for a condition for which it was not prescribed. Do not give LOVAZA to other people, even if they have the same problem you have. It may harm them.

This leaflet summarizes the most important information about LOVAZA. If you would like more information, talk with your doctor. You can ask your doctor or pharmacist for information about LOVAZA that is written for health professionals or go to www.LOVAZA.com.

What are the ingredients in LOVAZA?

Active Ingredient: Omega-3-acid ethyl esters

Inactive Ingredients: Gelatin, glycerol, purified water, alpha-tocopherol (in soybean oil)

LOVAZA is a registered trademark of the GlaxoSmithKline group of companies.

PLAVIX is a registered trademark of Sanofi-Synthelabo.

Manufactured for GlaxoSmithKline by:

Catalent Pharma Solutions

2725 Scherer Drive

St. Petersburg, FL 33716-1016

Accucaps Industries Limited

2125 Ambassador Drive

Windsor, Ontario, Canada N9B 3R5

Banner Pharmaceuticals Inc.

4125 Premier Drive

High Point, NC 27265

Distributed by:

GlaxoSmithKline

Research Triangle Park, NC 27709

©2009 GlaxoSmithKline. All rights reserved.

September 2009 LVZ:2PIL

Repackaged by:

Rebel Distributors Corp

Thousand Oaks, CA 91320

PACKAGE LABEL

PRINCIPAL DISPLAY PANEL